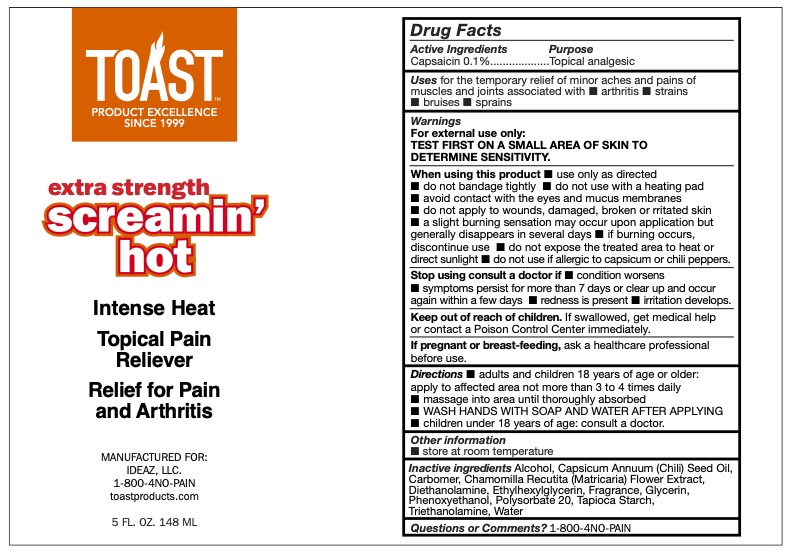 DRUG LABEL: Toast Screamin Hot
NDC: 78983-102 | Form: CREAM
Manufacturer: IDEAZ, LLC
Category: otc | Type: HUMAN OTC DRUG LABEL
Date: 20251212

ACTIVE INGREDIENTS: CAPSAICIN 0.1 g/100 g
INACTIVE INGREDIENTS: GLYCERIN; TRIETHANOLAMINE; PHENOXYETHANOL; WATER; CAPSICUM ANNUUM WHOLE; DIETHANOLAMINE; ETHYLHEXYLGLYCERIN; ALCOHOL; CARBOMER 940; POLYSORBATE 20; TAPIOCA STARCH; MATRICARIA CHAMOMILLA FLOWERING TOP OIL

Toast Extra Strength Screamin' Hot - 78983-102

Active Ingredient

Capsaicin 0.1%

Purpose

Topical analgesic

Uses

for the temporary relief of minor aches and pains of

muscles and joints associated with ■ arthritis ■ strains

■ bruises ■ sprains

Warnings

For external use only:

TEST FIRST ON A SMALL AREA OF SKIN TO

DETERMINE SENSITIVITY.

When using this product

■ use only as directed

■ do not bandage tightly ■ do not use with a heating pad

■ avoid contact with the eyes and mucus membranes

■ do not apply to wounds, damaged, broken or rritated skin

■ a slight burning sensation may occur upon application but

generally disappears in several days ■ if burning occurs,

discontinue use ■ do not expose the treated area to heat or

direct sunlight ■ do not use if allergic to capsicum or chili peppers.

Stop using consult a doctor if

■ condition worsens

■ symptoms persist for more than 7 days or clear up and occur

again within a few days ■ redness is present ■ irritation develops.

Keep out of reach of children

If swallowed, get medical help

or contact a Poison Control Center immediately.

If pregnant or breast-feeding

ask a healthcare professional before use.

Directions

■ adults and children 18 years of age or older:

apply to affected area not more than 3 to 4 times daily

■ massage into area until thoroughly absorbed

■ WASH HANDS WITH SOAP AND WATER AFTER APPLYING

■ children under 18 years of age: consult a doctor.

Other information

■ store at room temperature

Inactive ingredients

Alcohol, Capsicum Annuum (Chili) Seed Oil, Carbomer, Chamomilla Recutita (Matricaria) Flower Extract, Diethanolamine, Ethylhexylglycerin, Fragrance, Glycerin, Phenoxyethanol, Polysorbate 20, Tapioca Starch, Triethanolamine, Water

Questions or Comments?

1-800-4NO-PAIN